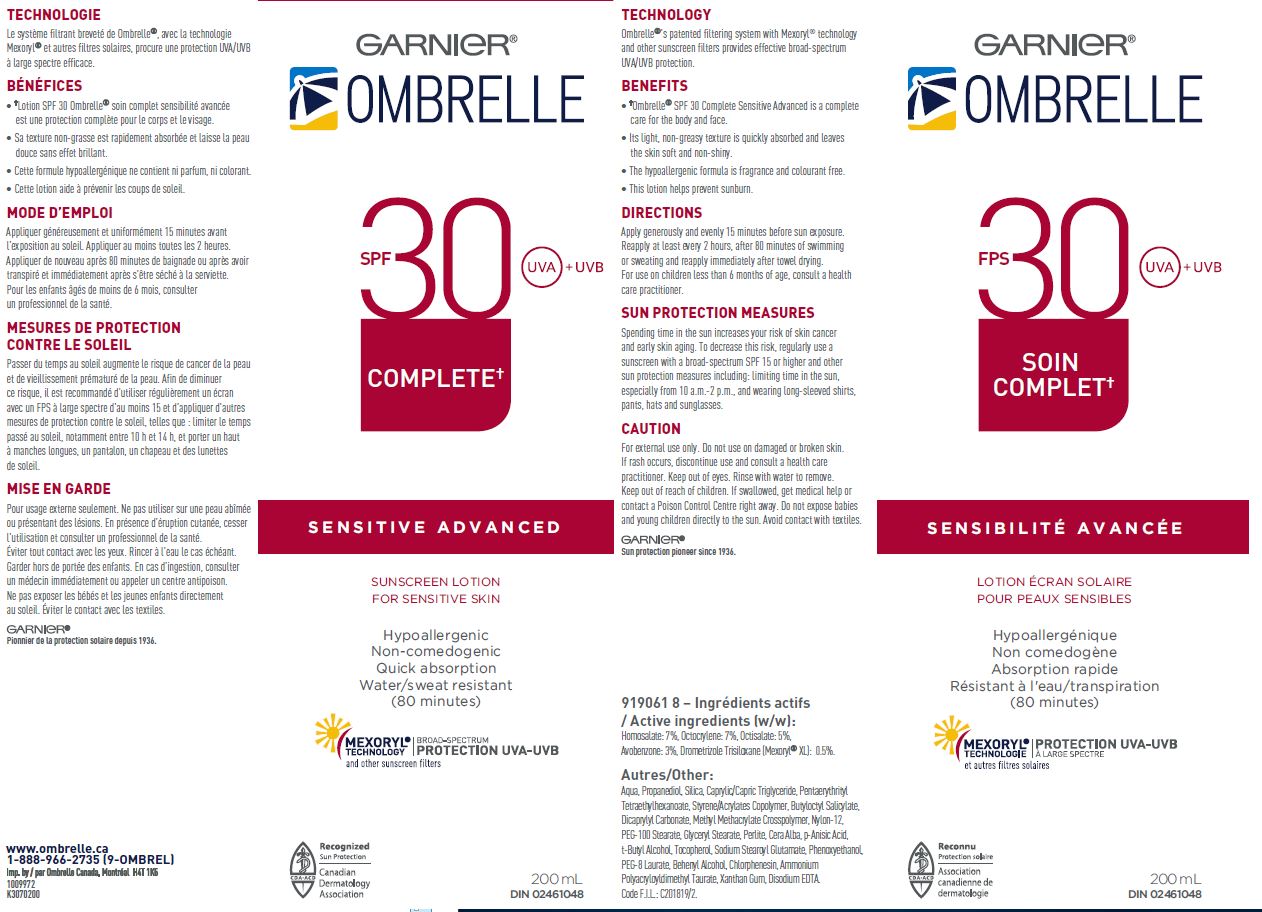 DRUG LABEL: Garnier Ombrelle SPF 30 Complete UVA UVB Sensitive Advanced Sunscreen for Sensitive Skin Hypoallergenic Non comedogenic Quick Absorption Water/sweat resistant 80 minutes
NDC: 49967-755 | Form: LOTION
Manufacturer: L'Oreal USA Products Inc
Category: otc | Type: HUMAN OTC DRUG LABEL
Date: 20260107

ACTIVE INGREDIENTS: homosalate 70 mg/1 mL; OCTOCRYLENE 70 mg/1 mL; OCTISALATE 50 mg/1 mL; AVOBENZONE 30 mg/1 mL; DROMETRIZOLE TRISILOXANE 5 mg/1 mL
INACTIVE INGREDIENTS: WATER; PROPANEDIOL; SILICON DIOXIDE; MEDIUM-CHAIN TRIGLYCERIDES; PENTAERYTHRITYL TETRAETHYLHEXANOATE; BUTYLOCTYL SALICYLATE; DICAPRYLYL CARBONATE; METHYL METHACRYLATE/GLYCOL DIMETHACRYLATE CROSSPOLYMER; NYLON-12; PEG-100 STEARATE; GLYCERYL MONOSTEARATE; PERLITE; WHITE WAX; P-ANISIC ACID; CHLORPHENESIN; EDETATE DISODIUM; DOCOSANOL; PEG-8 LAURATE; PHENOXYETHANOL; SODIUM STEAROYL GLUTAMATE; TERT-BUTYL ALCOHOL; TOCOPHEROL; XANTHAN GUM; AMMONIUM POLYACRYLOYLDIMETHYL TAURATE (55000 MPA.S)

Drug facts

Active ingredients

Homosalate 7%
Octocrylene 7%
Octisalate 5%
Avobenzone 3%
Drometrizole Trisiloxane 0.5%

Other

Aqua, Propanediol, Silica, Caprylic/Capric Triglyceride, Pentaerythrityl Tetraethylhexanoate, Styrene/acrylates Copolymer, Butyloctyl Salicylate, Dicaprylyl Carbonate, Methyl Methacrylate Crosspolymer, Nylon-12, PEG-100 Stearate, Glyceryl Stearate, Perlite, Cara Alba, p-Anisic Acid, t-Butyl Alcohol, Tocopherol, Sodium Stearoyl Glutamate, Phenoxyethanol, PEG-8 Laurate, Behenyl Alcohol, Chlorphenesin, Ammonium Polyacryloylmethyl Taurate, Xanthan Gum Disodium EDTA

Technology

Ombrelle’s patented filtering system with Mexoryl technology and other sunscreen filters provides effective broad-spectrum UVA/UVB protection.

Directions

Apply generously and evenly 15 minutes before sun exposure. Reapply at least every 2 hours, after 80 minutes of swimming or sweating and immediately after towel drying. For use on children less than 6 months of age, consult a health care practitioner.

SUN PROTECTION MEASURES
Spending time in the sun increases your risk of skin cancer and early skin aging. To decrease this risk, regularly use a sunscreen with a Broad Spectrum SPF value of 15 or higher and other sun protection measures including: limiting time in the sun, especially from 10 a.m. – 2 p.m., and wearing long-sleeved shirts, pants, hats, and sunglasses.

Caution

For external use only. Do not use on damaged or broken skin. If rash occurs, discontinue use and consult a health care practitioner. Keep product out of eyes. IF contact occurs, rinse with water to remove. Keep out of reach of children. If swallowed, get medical help or contact a Poison Control Centre right away. Do not expose babies and young children directly to the sun. Avoid contact with textiles.